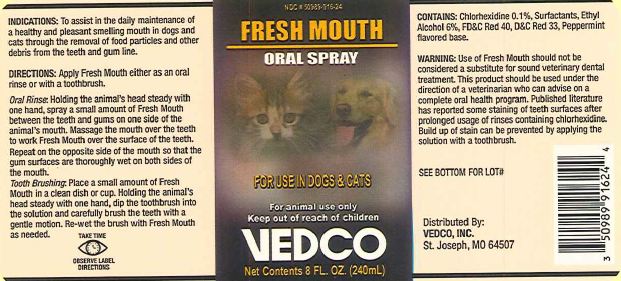 DRUG LABEL: Fresh Mouth
NDC: 50989-916 | Form: SPRAY
Manufacturer: Vedco, Inc
Category: animal | Type: OTC ANIMAL DRUG LABEL
Date: 20120606

ACTIVE INGREDIENTS: CHLORHEXIDINE GLUCONATE 1.000 mg/1.0 L
INACTIVE INGREDIENTS: ALCOHOL 60.000 mg/1.0 L

Fresh Mouth

Indications:

To assist in the daily maintenance of a healthy and pleasant smelling mouth in dogs and cats through the removal of food particles and other debris from the teeth and gum line.

Directions:

Apply Fresh Mouth either as an oral rinse or with a toothbrush.

Oral Rinse: Holding the animal's head steady with one hand, spray a small amount of Fresh Mouth between the teeth and gums on one side of the animal's mouth. Massage the mouth over the teeth to work Fresh Mouth over the surface of the teeth. Repeat on the opposite side of the mouth so that the gum surfaces are thoroughly wet on both sides of the mouth.

Tooth Brushing: Place a small amount of Fresh Mouth in a clean dish or cup. Holding the animal's head steady with one hand, dip the toothbrush into the solution and carefully brush the teeth with a gentle motion. Re-wet the brush with Fresh Mouth as needed.

For Animal Use Only

For Use in Dogs & Cats

Active Ingredient:

Chlorhexidine 0.1%

Warning:

Use of Fresh Mouth should not be considered a substitute for sound veterinary dental treatment. This product should be used under the direction of a veterinarian who can advise on a complete oral health program. Published literature has reported some staining on teeth surfaces after prolonged use of rinses containing chlorhexidine. Build up of stain can be prevented by applying the solution with a toothbrush.

Inactive Ingredients:

Surfactants, Ethyl Alcohol 6%, FD&C Red 40, D&C Red 33, Peppermint flavored base.

Principle Display Panel

Fresh Mouth Oral Spray